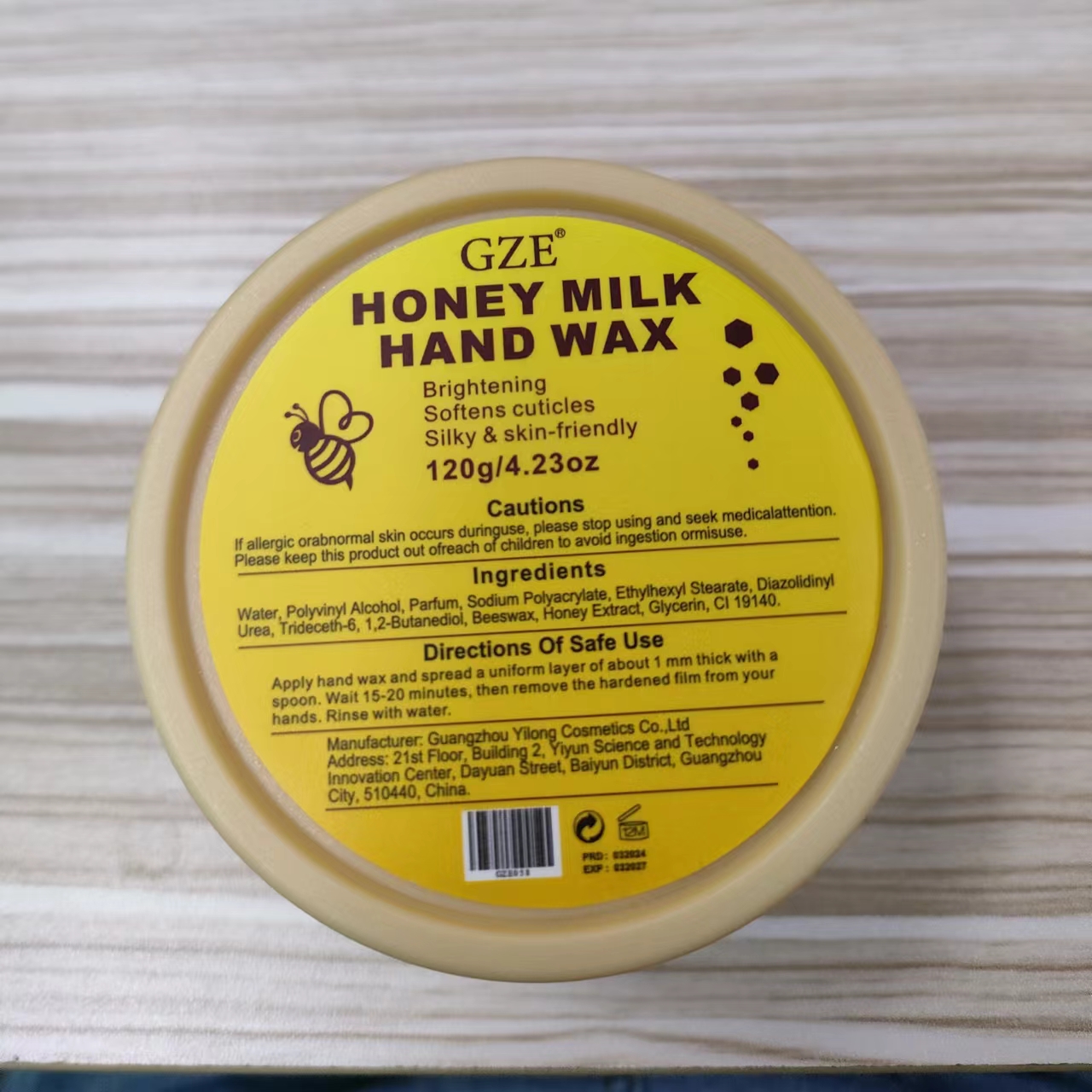 DRUG LABEL: GZE HONEY MILK HAND WAX
NDC: 74458-058 | Form: PASTE
Manufacturer: Guangzhou Yilong Cosmetics Co., Ltd
Category: otc | Type: HUMAN OTC DRUG LABEL
Date: 20241108

ACTIVE INGREDIENTS: HONEY EXTRACT 5 g/100 g; BEESWAX 5 g/100 g
INACTIVE INGREDIENTS: WATER; 1,2-BUTANEDIOL; POLYVINYL ALCOHOL; ETHYLHEXYL STEARATE; SODIUM POLYACRYLATE (8000 MW); TRIDECETH-6; DIAZOLIDINYL UREA; GLYCERIN; CI 19140

GZE HONEY MILK HAND WAX

INACTIVE INGREDIENT

Water

Polyvinyl Alcohol

Parfum

Sodium Polyacrylate

Ethylhexyl Stearate

Diazolidinyl Urea

Trideceth-6

1,2-Butanediol

Glycerin

CI 19140

ACTIVE INGREDIENT

Beewax

Honey Extract

PURPOSE

Exfoliation.

INDICATIONS AND USAGE

Apply hand wax and spread a uniform layer of about 1 mm thick with a spoon.Wait 15-20 minutes, then remove the hardened film from your hands.

WARNINGS

For external use only.

Stop use and ask a doctor if rash occurs.

Do not use on damaged or broken skin.

When using this product keep out of eyes. Rinse with water to remove.

Keep out of reach of children. If swallowed, get medical help or contact a Poison Control Center right away.

DOSAGE AND ADMINISTRATION

Apply hand wax and spread a uniform layer of about 1 mm thick with a spoon.Wait 15-20 minutes, then remove the hardened film from your hands.